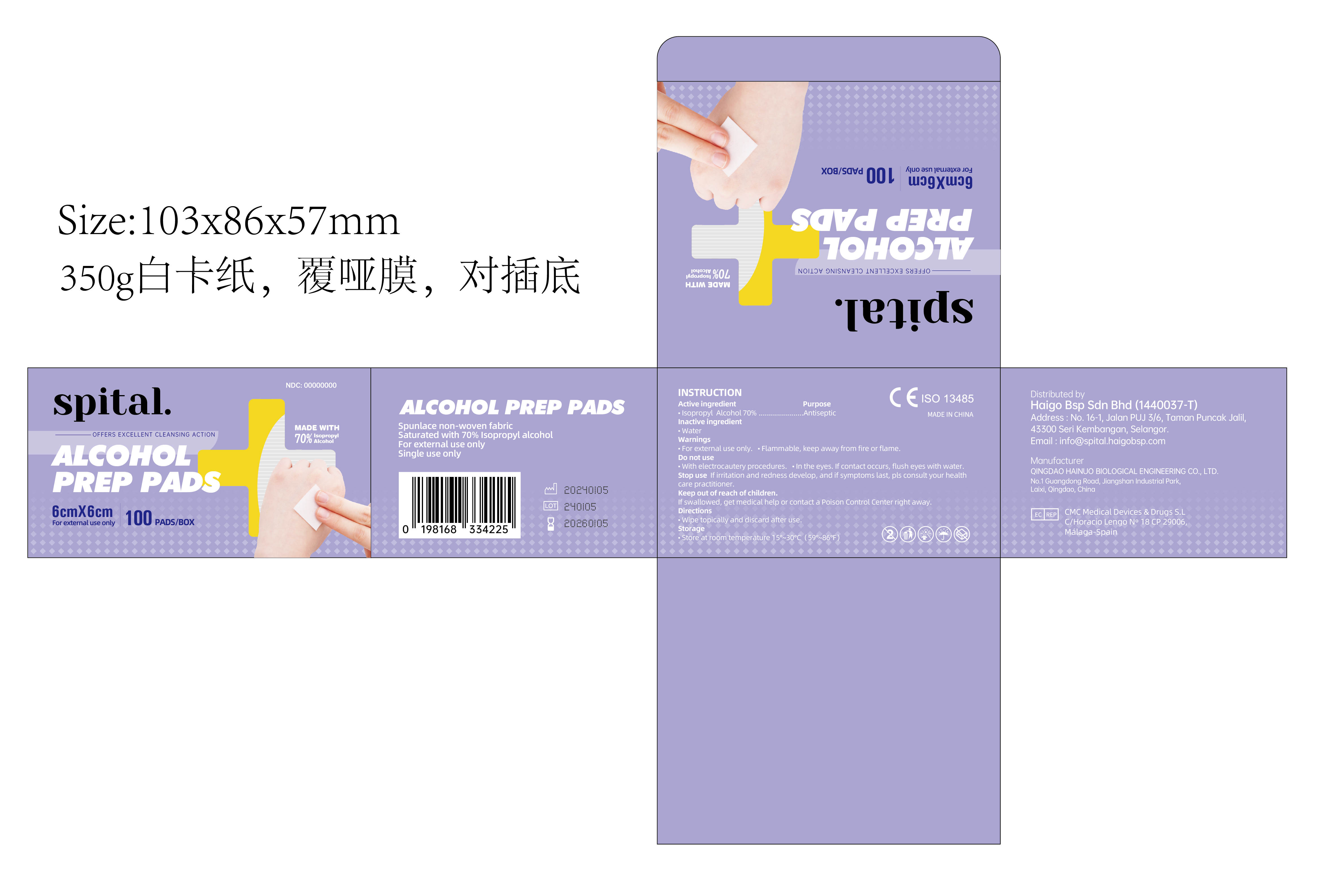 DRUG LABEL: spital. ALCOHOL PREP PADS
NDC: 84018-001 | Form: SWAB
Manufacturer: Haigo Bsp Sdn Bhd
Category: otc | Type: HUMAN OTC DRUG LABEL
Date: 20240122

ACTIVE INGREDIENTS: ISOPROPYL ALCOHOL 70 mL/100 mL
INACTIVE INGREDIENTS: WATER

84018-001
spital. ALCOHOL PREP PADS

ACTIVE INGREDIENT

Isopropyl Alcohol 70%......................Antiseptic

PURPOSE

Antiseptic

Warnings

- For external use only.
- Flammable, keep away from fire or flame.

Do not use

- with electrocautery procedures.
- in the eyes. If contact occurs, flush eyes with water.

Stop use

if irritation and redness develop， and if symptoms last，pls consult your health care practitioner.

Keep out of reach of children

If swallowed, get medical help or contact a Poison Control Center right away

Directions

Wipe topically and discard after use.

Storage

Store at room temperature 10℃~30℃（59°F~86°F）

INACTIVE INGREDIENT

Water

PACKAGE LABEL

84018-001-01